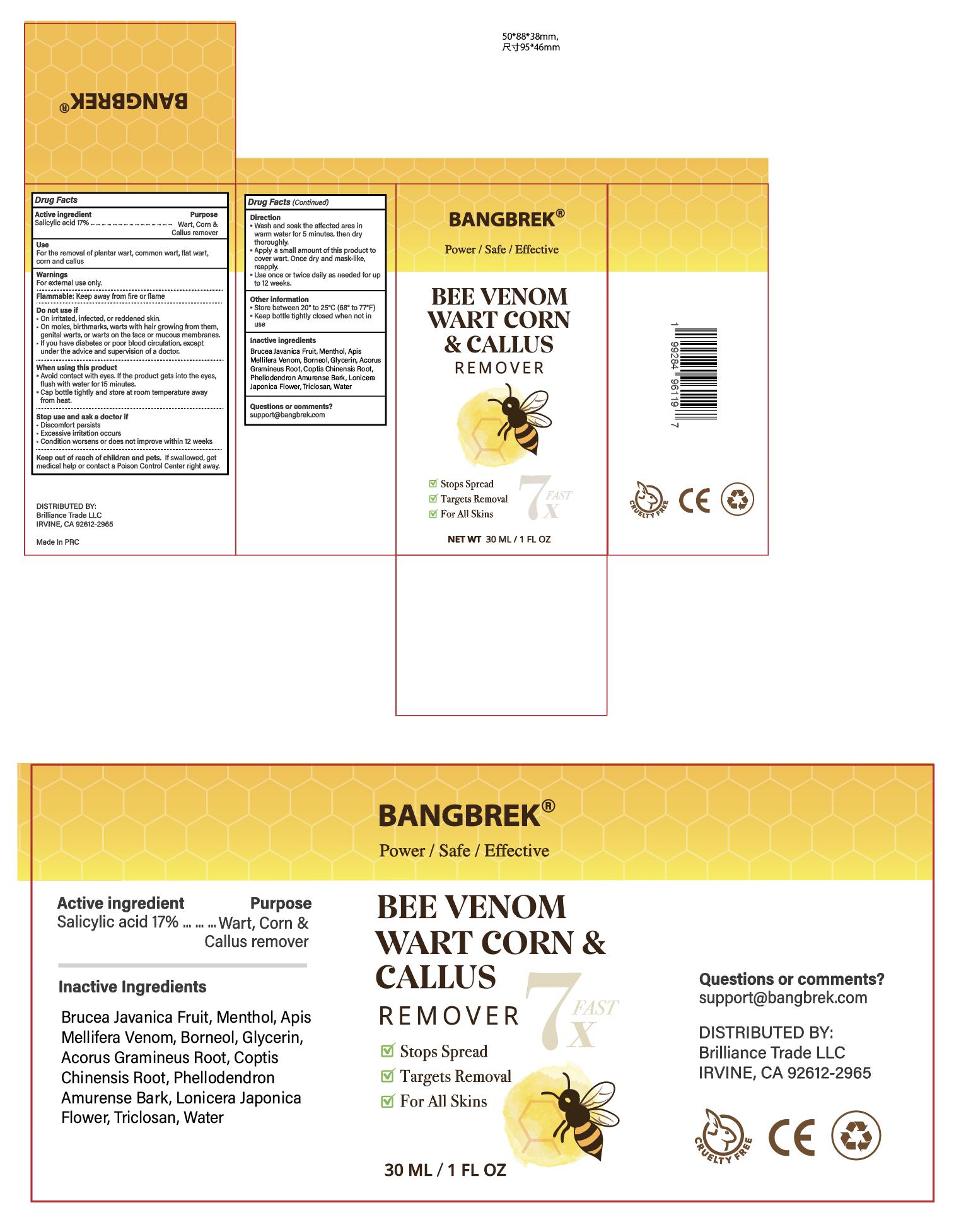 DRUG LABEL: Bangbrek Bee Venom Wart Corn Callus Remover
NDC: 85792-001 | Form: LIQUID
Manufacturer: Brilliance Trade LLC
Category: otc | Type: HUMAN OTC DRUG LABEL
Date: 20250620

ACTIVE INGREDIENTS: SALICYLIC ACID 17 mg/1 mL
INACTIVE INGREDIENTS: BRUCEA JAVANICA FRUIT; MENTHOL; APIS MELLIFERA VENOM; BORNEOL; GLYCERIN; ACORUS GRAMINEUS ROOT; COPTIS CHINENSIS ROOT; PHELLODENDRON AMURENSE BARK; LONICERA JAPONICA FLOWER; TRICLOSAN; WATER

Initial Drug Listing - Bangbrek Bee Venom Wart Corn & Callus Remover

Active ingredient:

1. Salicylic acid 17%

PURPOSE

1. Wart, corn, and callus remover

INDICATIONS AND USAGE

For the removal of

1. plantar wart
2. common wart
3. flat wart
4. corn and callus

WARNINGS

For external use only

Flammable: Keep away from fire or flame

Do not use:

- On irritated, infected, or reddened skin.
- On moles, birthmarks, warts with hair growing from them, genital warts, or warts on the face or mucous membranes.
- If you have diabetes or poor blood circulation, except under the advice and supervision of a doctor.

When using this product

Avoid contact with eyes. If the product gets into the eyes,flush with water for 15 minutes.

Cap bottle tightly and store at room temperature away from heat.

Stop use and ask a doctor if

- Discomfort persists
- Excessive irritation occurs
- Condition worsens or does not improve within 12 weeks

Keep out of reach of children and pets.

If swallowed,get medical help or contact a Poison Control Center right away.

Directions:

- Wash and soak the affected area in warm water for 5 minutes, then dry thoroughly.
- Apply a small amount of this product to cover wart. Once dry and mask-like, reapply.
- Use once or twice daily as needed for up to 12 weeks.

Other information:

- Store between 20° to 25°C (68° to 77°F)
- Keep bottle tightly closed when not in use

Inactive ingredients:

- BRUCEA JAVANICA FRUIT
- MENTHOL
- APIS MELLIFERA VENOM
- BORNEOL
- GLYCERIN
- ACORUS GRAMINEUS ROOT
- COPTIS CHINENSIS ROOT
- PHELLODENDRON AMURENSE BARK
- LONICERA JAPONICA FLOWER
- TRICLOSAN
- WATER

Questions or comments?

support@bangbrek.com

PACKAGE LABEL.PRINCIPAL DISPLAY PANEL

Available in 30 mL, 20 mL, 15 mL, and 10 mL box. All packages look the same externally, with the only variation being fill volume.